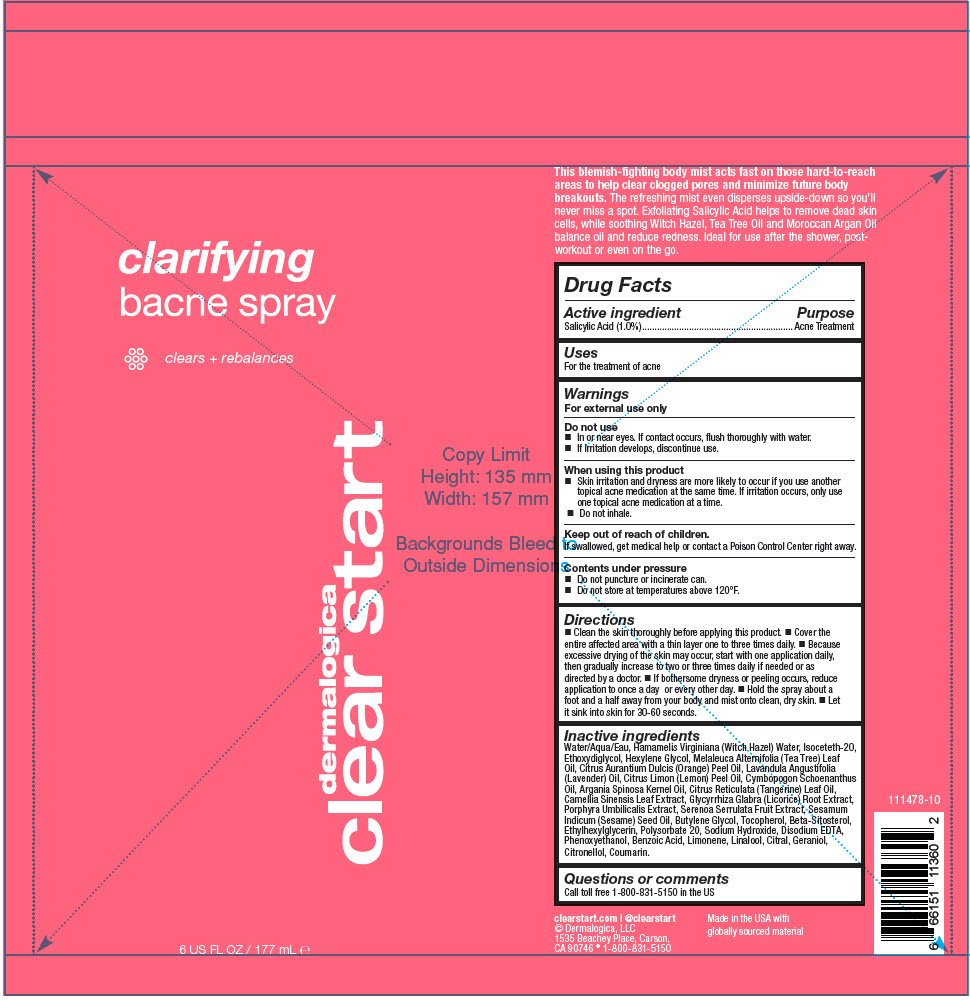 DRUG LABEL: Clarifying Bacne
NDC: 68479-782 | Form: SPRAY
Manufacturer: Dermalogica, LLC.
Category: otc | Type: HUMAN OTC DRUG LABEL
Date: 20250102

ACTIVE INGREDIENTS: Salicylic Acid 1 g/100 mL
INACTIVE INGREDIENTS: Water; HAMAMELIS VIRGINIANA TOP WATER; Isoceteth-20; DIETHYLENE GLYCOL MONOETHYL ETHER; Hexylene Glycol; Phenoxyethanol; Polysorbate 20; ORANGE OIL, COLD PRESSED; Sodium Hydroxide; TEA TREE OIL; Ethylhexylglycerin; LAVENDER OIL; EDETATE DISODIUM ANHYDROUS; Butylene Glycol; LEMON OIL, DISTILLED; Cymbopogon Schoenanthus Oil; ARGAN OIL; Benzoic Acid; CITRUS AURANTIUM FRUIT OIL; SESAME OIL; GREEN TEA LEAF; GLYCYRRHIZA GLABRA; PORPHYRA UMBILICALIS; Tocopherol; .BETA.-SITOSTEROL; SAW PALMETTO; LIMONENE, (+)-; LINALOOL, (+/-)-; CITRAL; Geraniol; .BETA.-CITRONELLOL, (R)-; Coumarin

Clarifying Bacne Spray

Drug Facts

Active ingredient

Salicylic Acid (1.0%)

Purpose

Acne Treatment

Uses

For the treatment of acne

Warnings

For external use only

Do not use

- In or near eyes. If contact occurs, flush thoroughly with water.
- If irritation develops, discontinue use.

When using this product

- Skin irritation and dryness are more likely to occur if you use another topical acne medication at the same time. If irritation occurs, only use one topical acne medication at a time.
- Do not inhale.

Keep out of reach of children.

If swallowed, get medical help or contact a Poison Control Center right away.

Contents under pressure

- Do not puncture or incinerate can.
- Do not store at temperatures above 120°F.

Directions

- Clean the skin thoroughly before applying this product.
- Cover the entire affected area with a thin layer one to three times daily.
- Because excessive drying of the skin may occur, start with one application daily, then gradually increase to two or three times daily if needed or as directed by a doctor.
- If bothersome dryness or peeling occurs, reduce application to once a day or every other day.
- Hold the spray about a foot and a half away from your body and mist onto clean, dry skin.
- Let it sink into skin for 30-60 seconds.

Inactive ingredients

Water/Aqua/Eau, Hamamelis Virginiana (Witch Hazel) Water, Isoceteth-20, Ethoxydiglycol, Hexylene Glycol, Melaleuca Alternifolia (Tea Tree) Leaf Oil, Citrus Aurantium Dulcis (Orange) Peel Oil, Lavandula Angustifolia (Lavender) Oil, Citrus Limon (Lemon) Peel Oil, Cymbopogon Schoenanthus Oil, Argania Spinosa Kernel Oil, Citrus Reticulata (Tangerine) Leaf Oil, Camellia Sinensis Leaf Extract, Glycyrrhiza Glabra (Licorice) Root Extract, Porphyra Umbilicalis Extract, Serenoa Serrulata Fruit Extract, Sesamum Indicum (Sesame) Seed Oil, Butylene Glycol, Tocopherol, Beta-Sitosterol, Ethylhexylglycerin, Polysorbate 20, Sodium Hydroxide, Disodium EDTA, Phenoxyethanol, Benzoic Acid, Limonene, Linalool, Citral, Geraniol, Citronellol, Coumarin.

Questions or comments

Call toll free 1-800-831-5150 in the US

PRINCIPAL DISPLAY PANEL - 177 mL Bottle Label

clarifying
bacne spray

clears + rebalances

dermalogica
clear start

6 US FL OZ / 177 mL ℮